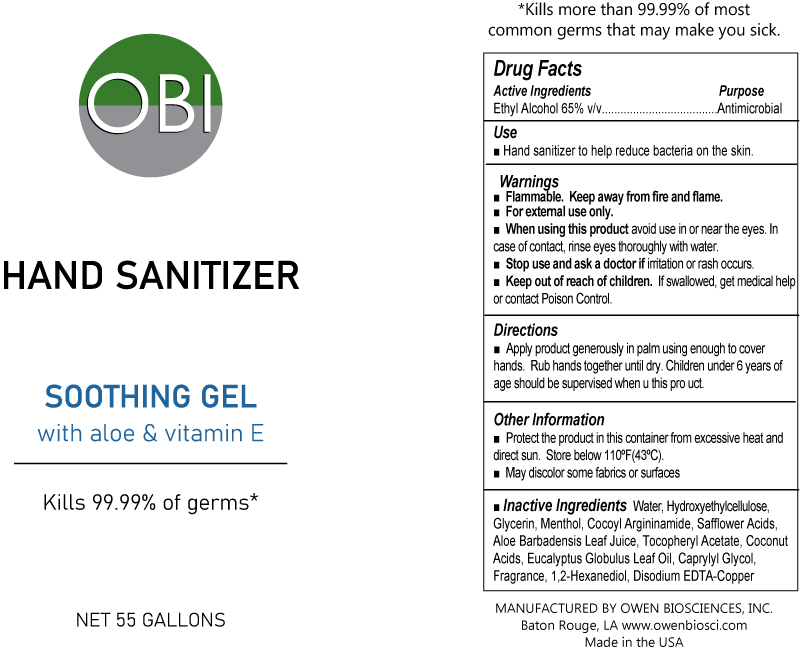 DRUG LABEL: Hand Sanitizer with Aloe
NDC: 59958-500 | Form: GEL
Manufacturer: Owen Biosciences, Inc.
Category: otc | Type: HUMAN OTC DRUG LABEL
Date: 20250113

ACTIVE INGREDIENTS: ALCOHOL 65 g/100 g
INACTIVE INGREDIENTS: WATER 30 g/100 g

Hand Sanitizer wth Aloe 185,000g

Drug Facts

Active Ingredients Purpose
Ethyl Alcohol 65% v/v....................Antimicrobial

Use

■ Hand sanitizer to help reduce bacteria on the skin

Use

■ Hand sanitizer to help reduce bacteria on the skin

Warnings

■ For external use only.
■ When using this product avoid use in or near the
eyes. In case of contact, rinse eyes thoroughly with
water.
■ Stop use and ask a doctor if irritation or rash occurs.
■ Keep out of reach of children. If swallowed, get
medical help or contact Poison Control.

■ Flammable. Keep away from fire and flame.

warnings

■ For external use only.
■ When using this product avoid use in or near the
eyes. In case of contact, rinse eyes thoroughly with
water.
■ Stop use and ask a doctor if irritation or rash occurs.
■ Keep out of reach of children. If swallowed, get
medical help or contact Poison Control.

■ Flammable. Keep away from fire and flame.

Directions

■ Apply product generously in palm using enough to
cover hands. Rub hands together until dry. Children
under 6 years of age should be supervised when using
this product.

Other information

■ Protect the product in this container from excessive
heat and direct sun. Store below 110ºF(43ºC).
■ May discolor some fabrics or surfaces

Inactive ingredients

Water, Hydroxyethylcellulose,
Glycerin, Menthol, Cocoyl Argininamide, Safflower Acids,
Aloe Barbadensis Leaf Juice, Tocopheryl Acetate, Coconut
Acids, Eucalyptus Globulus Leaf Oil, Caprylyl Glycol,
Fragrance, 1,2-Hexanediol, Disodium EDTA-Copper